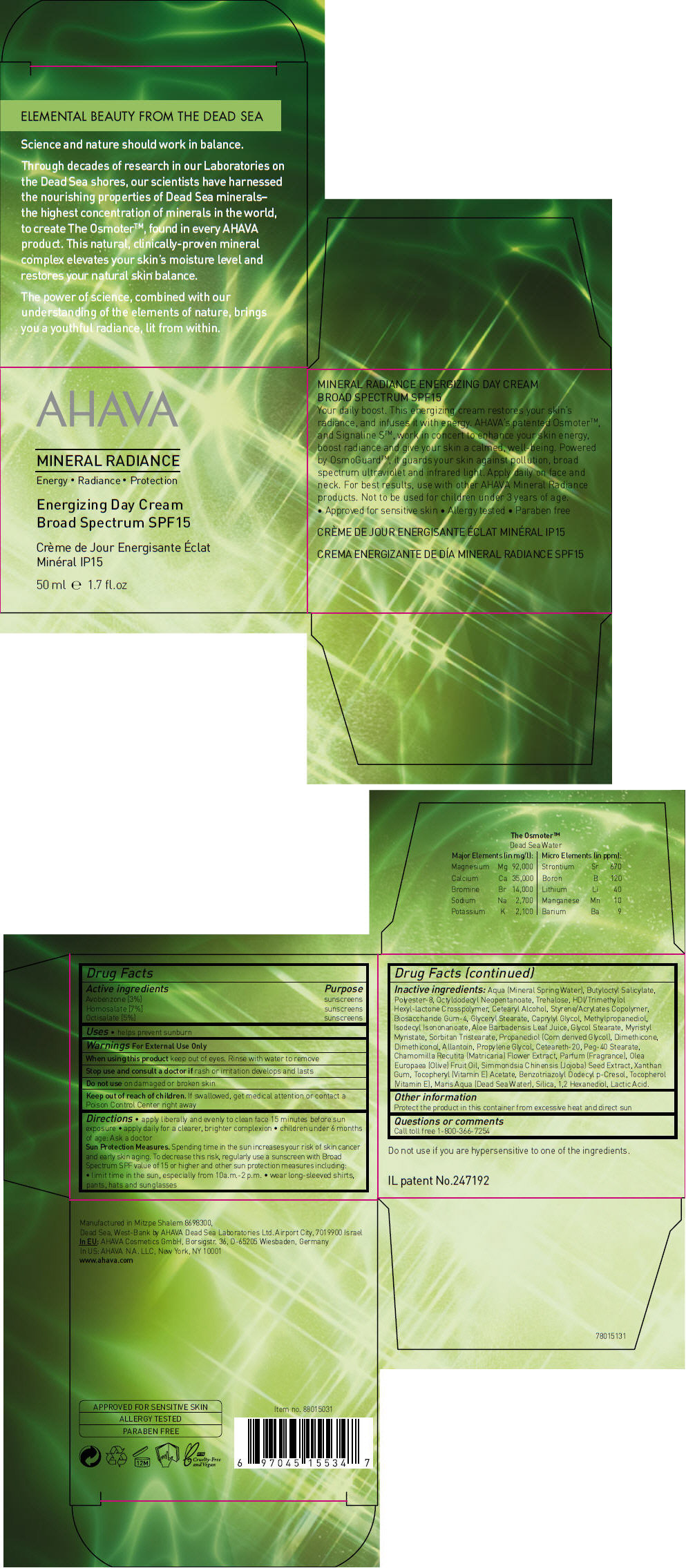 DRUG LABEL: Mineral Radiance Energizing Day BS SPF 15
NDC: 60289-284 | Form: CREAM
Manufacturer: AHAVA Dead Sea Laboratories Ltd
Category: otc | Type: HUMAN OTC DRUG LABEL
Date: 20231108

ACTIVE INGREDIENTS: Avobenzone 30 mg/1 mL; Homosalate 70 mg/1 mL; Octisalate 50 mg/1 mL
INACTIVE INGREDIENTS: Water; Butyloctyl Salicylate; Polyester-8 (1400 MW, Cyanodiphenylpropenoyl Capped); Octyldodecyl Neopentanoate; Trehalose; Hexamethylene Diisocyanate/Trimethylol Hexyllactone Crosspolymer; Cetostearyl Alcohol; Biosaccharide Gum-4; Glyceryl Monostearate; Caprylyl Glycol; Methylpropanediol; Isodecyl Isononanoate; Aloe Vera Leaf; Glycol Stearate; Myristyl Myristate; Sorbitan Tristearate; Dimethicone; Allantoin; Propylene Glycol; Polyoxyl 20 Cetostearyl Ether; Peg-40 Stearate; Chamomile; Olive Oil; Simmondsia Chinensis Seed; Xanthan Gum; .Alpha.-Tocopherol Acetate; Benzotriazolyl Dodecyl p-Cresol; Tocopherol; Sodium Chloride; Silicon Dioxide; 1,2-Hexanediol; Lactic Acid, Unspecified Form

AHAVA MINERAL RADIANCE

Drug Facts

ACTIVE INGREDIENT

Active ingredients | Purpose
Avobenzone [3%] | sunscreens
Homosalate [7%] | sunscreens
Octisalate [5%] | sunscreens

Uses

- helps prevent sunburn

Warnings

For External Use Only

When using this product keep out of eyes. Rinse with water to remove

Stop use and consult a doctor if rash or irritation develops and lasts

Do not use on damaged or broken skin

Keep out of reach of children. If swallowed, get medical attention or contact a Poison Control Center right away

Directions

- apply liberally and evenly to clean face 15 minutes before sun exposure
- apply daily for a clearer, brighter complexion
- children under 6 months of age: Ask a doctor

Sun Protection Measures. Spending time in the sun increases your risk of skin cancer and early skin aging. To decrease this risk, regularly use a sunscreen with Broad Spectrum SPF value of 15 or higher and other sun protection measures including:

- limit time in the sun, especially from 10a.m.-2 p.m.
- wear long-sleeved shirts, pants, hats and sunglasses

Inactive ingredients

Aqua (Mineral Spring Water), Butyloctyl Salicylate, Polyester-8, Octyldodecyl Neopentanoate, Trehalose, HDI/Trimethylol Hexyl-lactone Crosspolymer, Cetearyl Alcohol, Styrene/Acrylates Copolymer, Biosaccharide Gum-4, Glyceryl Stearate, Caprylyl Glycol, Methylpropanediol, Isodecyl Isononanoate, Aloe Barbadensis Leaf Juice, Glycol Stearate, Myristyl Myristate, Sorbitan Tristearate, Propanediol (Corn derived Glycol), Dimethicone, Dimethiconol, Allantoin, Propylene Glycol, Ceteareth-20, Peg-40 Stearate, Chamomilla Recutita (Matricaria) Flower Extract, Parfum (Fragrance), Olea Europaea (Olive) Fruit Oil, Simmondsia Chinensis (Jojoba) Seed Extract, Xanthan Gum, Tocopheryl (Vitamin E) Acetate, Benzotriazolyl Dodecyl p-Cresol, Tocopherol (Vitamin E), Maris Aqua (Dead Sea Water), Silica, 1,2 Hexanediol, Lactic Acid.

Other information

Protect the product in this container from excessive heat and direct sun

Questions or comments

Call toll free 1-800-366-7254

PRINCIPAL DISPLAY PANEL - 50 ml Jar Carton

AHAVA

MINERAL RADIANCE
Energy • Radiance • Protection

Energizing Day Cream
Broad Spectrum SPF15

50 ml e 1.7 fl.oz